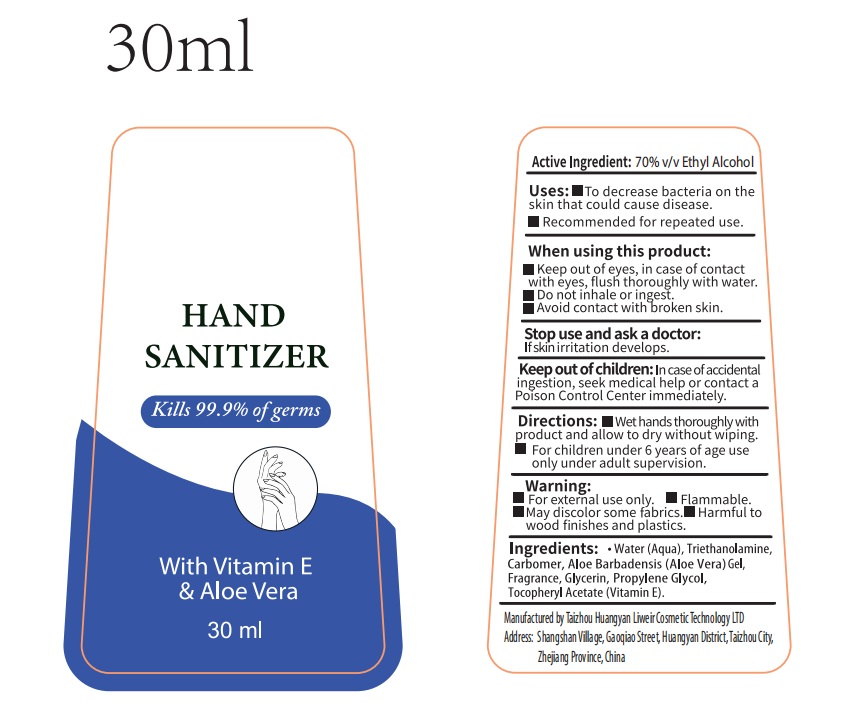 DRUG LABEL: HAND SANITIZER
NDC: 76860-002 | Form: SOLUTION
Manufacturer: Taizhou Huangyan Liweir Cosmetic Technology LTD
Category: otc | Type: HUMAN OTC DRUG LABEL
Date: 20200429

ACTIVE INGREDIENTS: ALCOHOL 70 mL/100 mL
INACTIVE INGREDIENTS: GLYCERIN; PROPYLENE GLYCOL; WATER; CARBOMER 934; ALOE VERA WHOLE; ALPHA-TOCOPHEROL ACETATE; TROLAMINE

NA

Active Ingredient(s)

Ethyl Alcohol 70% v/v

Purpose

Antimicrobial

Use

To decrease bacteria on the skin that could cause disease

Recommended for repeated use

Warnings

For external use only.

Flammable

May discolor some fabrics

Harmful to wood finishes and plastics

When using this product keep out of eyes. In case of contact with eyes, flush thoroughly with water.

Avoid contact with broken skin

Do not inhale or ingest

Stop use and ask a doctor if skin irritation develops

Keep out of reach of children. In case of accidental ingestion, seek medical help or contact a Poison Control Center immediately.

Directions

- Wet hands thoroughly with product and allow to dry without wiping
- For children under 6 years of age, use only under adult supervision

Inactive ingredients

Water, triethanolamin, carbomer, aloe barbadensis (aloe vera) gel, fragrance, propylene glycol, glycerin, tocopheryl acetate (Vitamin E)